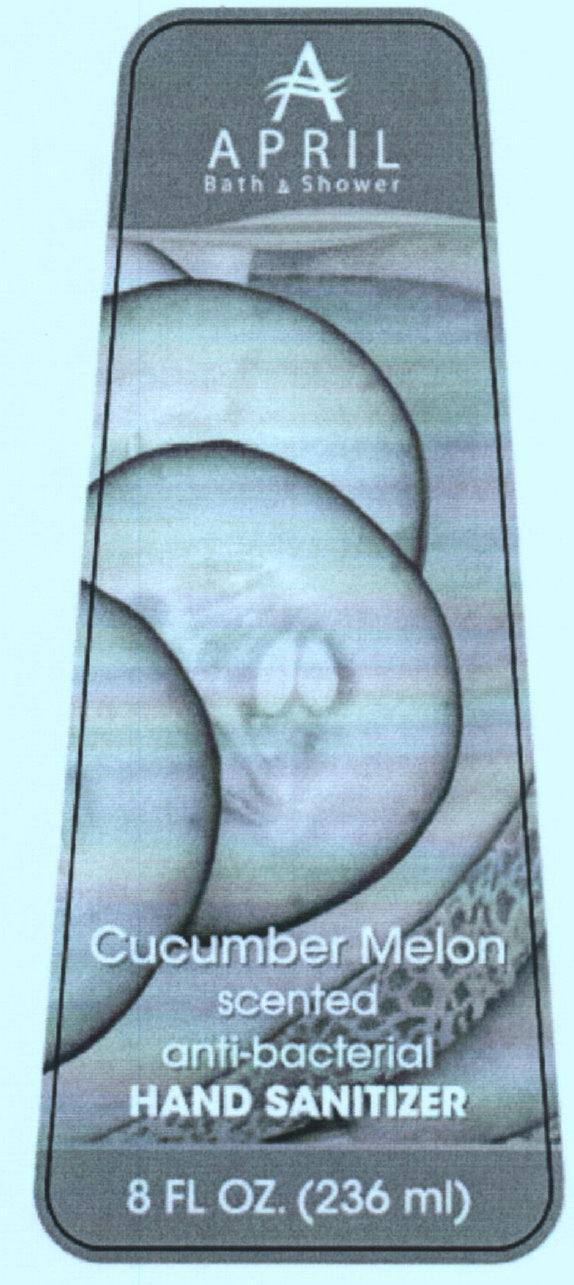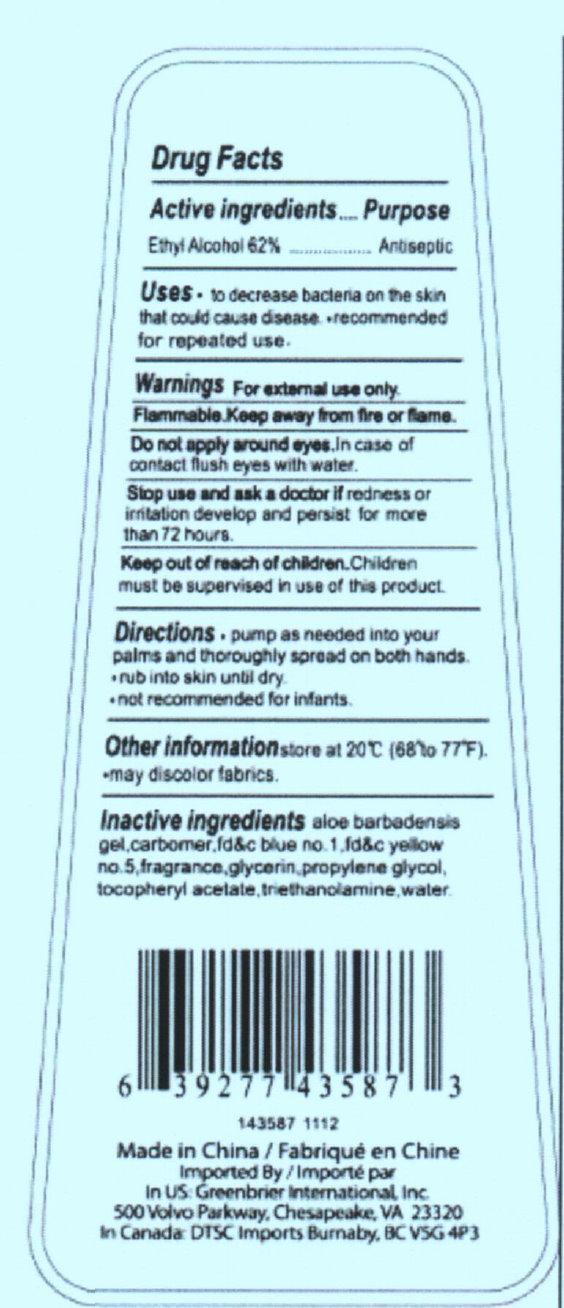 DRUG LABEL: APRIL Bath and Shower Cucumber Melon Scented Antibacterial HAND SANITIZER
NDC: 33992-4950 | Form: LIQUID
Manufacturer: Greenbrier International, Inc.
Category: otc | Type: HUMAN OTC DRUG LABEL
Date: 20150218

ACTIVE INGREDIENTS: ALCOHOL 62 mL/100 mL
INACTIVE INGREDIENTS: FD&C BLUE NO. 1; FD&C YELLOW NO. 5; GLYCERIN; PROPYLENE GLYCOL; ALPHA-TOCOPHEROL ACETATE; TROLAMINE; WATER

APRIL Bath and Shower Cucumber Melon Scented Antibacterial HAND SANITIZER

Active ingredients

Active ingredients...................Purpose
Ethyl Alcohol 62%................Antiseptic

Purpose

Antiseptic

Uses

• to decrease bacteria on the skin that could cause disease. • recommended for repeated use.

Warnings

For external use only. Flammable. Keep away from fire or flame.

Do not apply

around eyes. In case of contact flush eyes with water.

Stop Use and ask a doctor if

redness or irritation develop and persist for more than 72 hours.

Keep out of reach of children. Children must be supervised in use of this product.

Directions

• pump as needed into your palms and thoroughly spread on both hands. • rub into skin until dry. • not recommended for infants.

Other information

store at 20 degree C (68 degree to 77 degree F). • may discolor fabrics.

Inactive ingredients

aloe barbadensis gel, carbomer, fdandc blue no. 1, fdandc yellow no. 5, fragrance, glycerin, propylene glycol, tocopheryl acetate, triethanolamine, water.

Description

6 39277 43587 3 143587 1112 Made in China Imported By In US: Greenbrier International, Inc. 500 Volvo Parkway, Chesapeake, VA 23320 In Canada: DTSC Imports Burnaby, BC V5G 4P3

PACKAGE LABEL

A APRIL Bath and Shower Cucumber Melon Scented anti-bacterial HAND SANITIZER 8 FL OZ. (236 ml)

PACKAGE LABEL

Drug Facts Made in China Imported By In US: Greenbrier International, Inc. 500 Volvo Parkway, Chesapeake, VA 23320 In Canada: DTSC Imports Burnaby, BC V5G 4P3